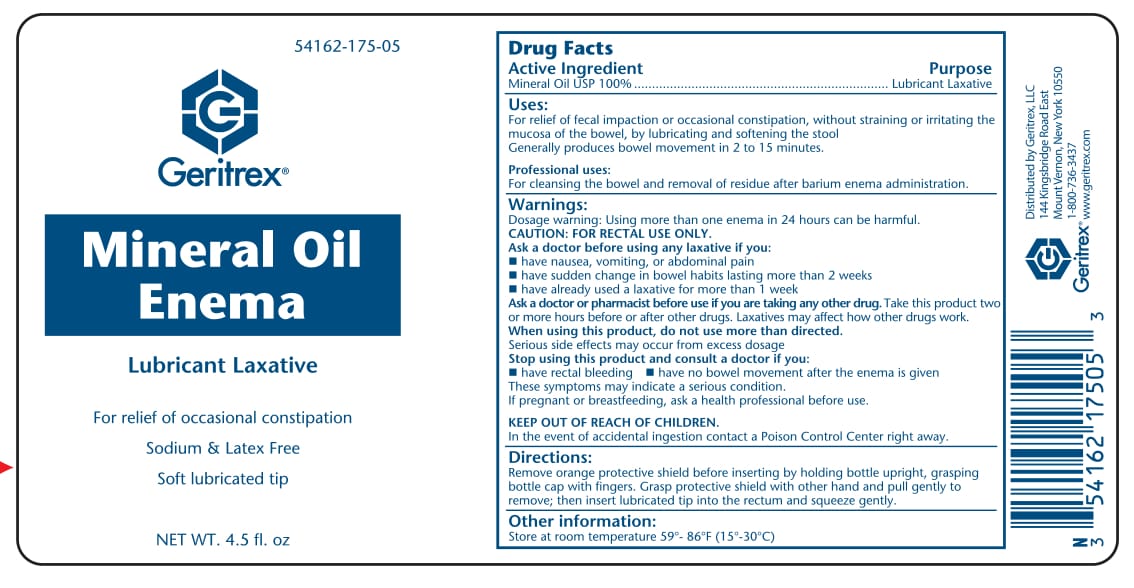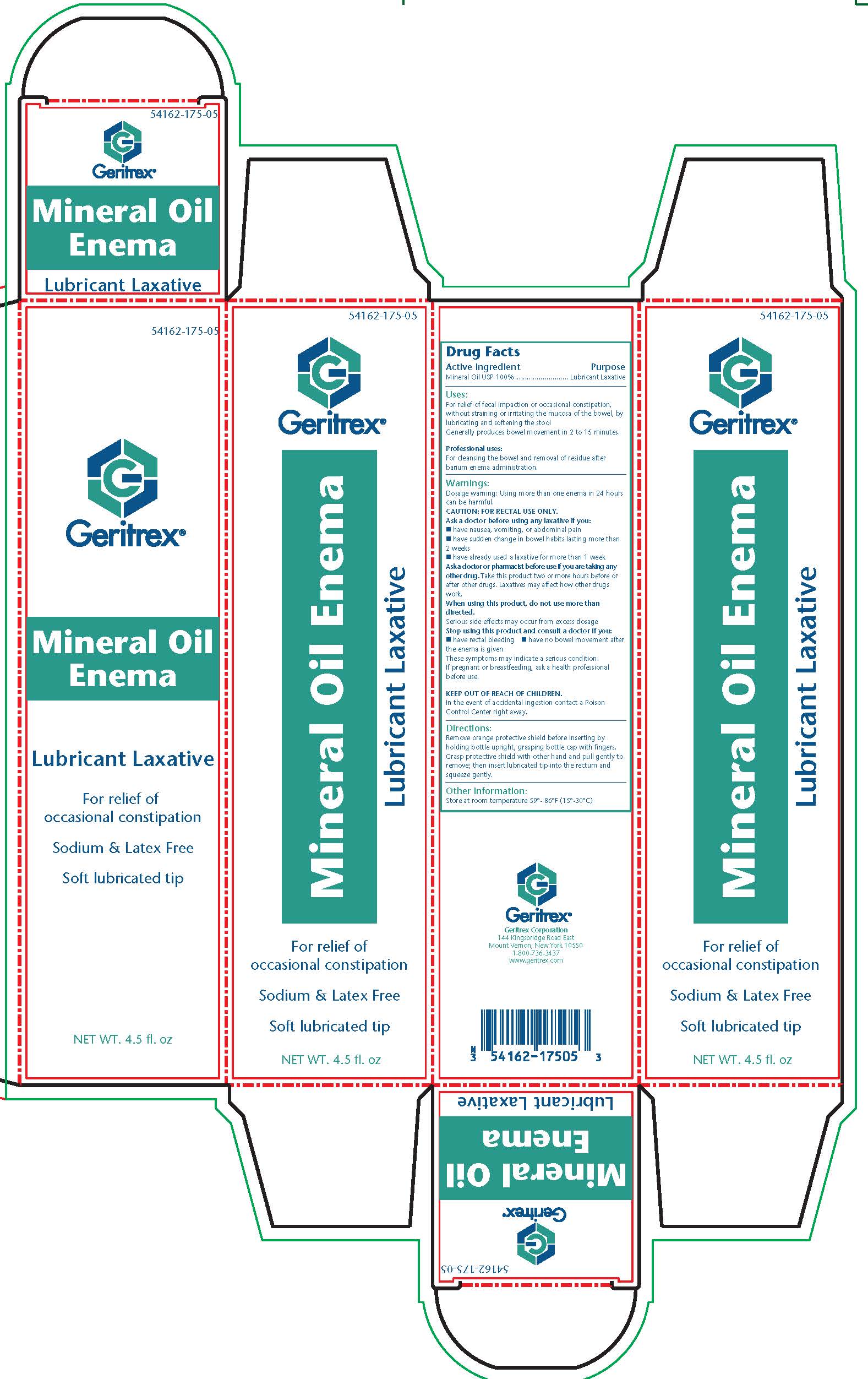 DRUG LABEL: Mineral oil
NDC: 54162-175 | Form: OIL
Manufacturer: GERITREX LLC
Category: otc | Type: HUMAN OTC DRUG LABEL
Date: 20170828

ACTIVE INGREDIENTS: MINERAL OIL 100 g/100 g
INACTIVE INGREDIENTS: VITAMIN D

Mineral Oil Enema

WARNINGS

Dosage wanring: Using more than one enema in 24 hours can be harmful
Caution: For rectal use only

Ask a doctor before using laxative if you:

- Have nausea, vomiting, or abdominal pain
- Have suddent change in bowel habits lasting more than two weeks
- Have already used a laxative for more than 1 week

Ask a doctor of pharmacist before use if you are taking any other drug. Take this product two or more hours before or after other drugs. Laxatives may affect how other drugs work.

When using this product, do not use more than directed.

Serious side effects may occur from excess dosage.

Stop using this product and consult a doctor if you:

- Have rectal bleeding
- Have no bowel movemenet after the enema is given

These symptoms may indicated a serious condition.

PREGNANCY OR BREAST FEEDING

If pregnant or breastfeeding Ask a health professional before use.

KEEP OUT OF REACH OF CHILDREN
In the case of accidental ingestion contact a Poison Control Center right away

DOSAGE AND ADMINISTRATION

Remove orange protective shield before inserting by holding bottle upright, grasping bottle cap with fingers. Grasp protective shield with other hand and pull gently to remove, then insert lubricated tip into rectum and squeeze gently.

STORAGE AND HANDLING

Store at room temperature 59°-86°F (15°-30°C)